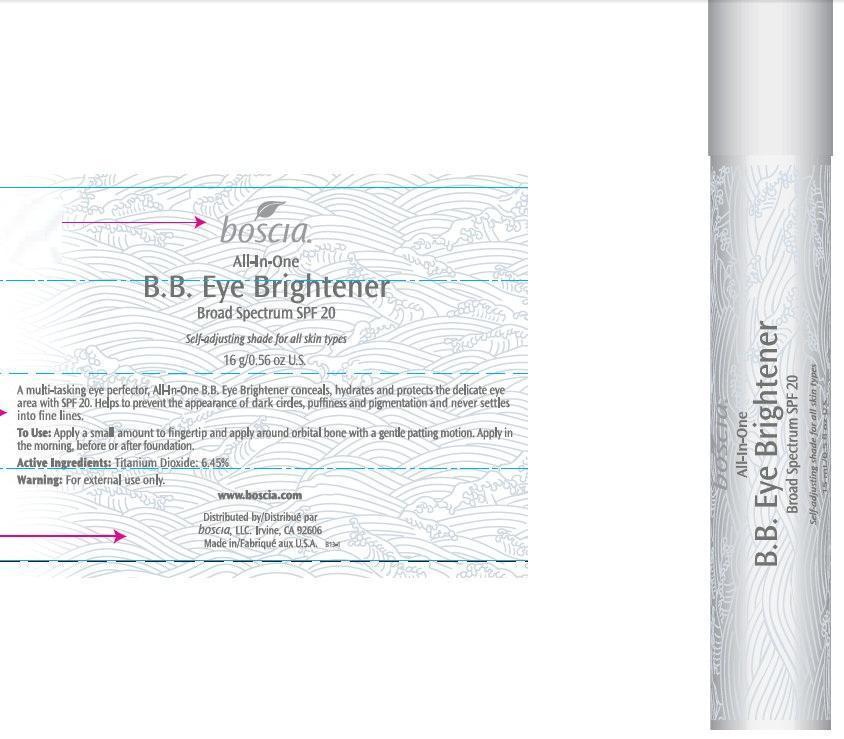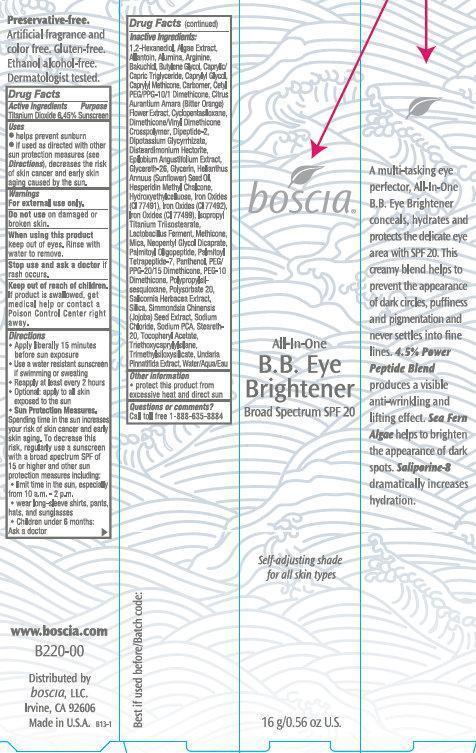 DRUG LABEL: Boscia All In One B.B. Eye Brightener Broad Spectrum SPF 20
NDC: 76151-261 | Form: CREAM
Manufacturer: Boscia LLC
Category: otc | Type: HUMAN OTC DRUG LABEL
Date: 20231212

ACTIVE INGREDIENTS: TITANIUM DIOXIDE 6.45 g/100 g
INACTIVE INGREDIENTS: 1,2-HEXANEDIOL; ALLANTOIN; ALUMINUM OXIDE; ARGININE; BAKUCHIOL; BUTYLENE GLYCOL; MEDIUM-CHAIN TRIGLYCERIDES; CAPRYLYL GLYCOL; CAPRYLYL TRISILOXANE; CITRUS AURANTIUM FLOWER; CYCLOMETHICONE 5; DIMETHICONE; VALYLTRYPTOPHAN; GLYCYRRHIZINATE DIPOTASSIUM; DISTEARDIMONIUM HECTORITE; GLYCERETH-26; GLYCERIN; SUNFLOWER OIL; HESPERIDIN METHYLCHALCONE; FERRIC OXIDE RED; FERRIC OXIDE YELLOW; FERROSOFERRIC OXIDE; ISOPROPYL TITANIUM TRIISOSTEARATE; MICA; NEOPENTYL GLYCOL DICAPRATE; PALMITOYL OLIGOPEPTIDE; PALMITOYL TETRAPEPTIDE-7; PANTHENOL; PEG/PPG-20/15 DIMETHICONE; POLYSORBATE 20; SALICORNIA EUROPAEA; SILICON DIOXIDE; SIMMONDSIA CHINENSIS SEED; SODIUM CHLORIDE; SODIUM PYRROLIDONE CARBOXYLATE; STEARETH-20; .ALPHA.-TOCOPHEROL ACETATE; TRIETHOXYCAPRYLYLSILANE; UNDARIA PINNATIFIDA; WATER

Boscia All In One B.B. Eye Brightener Broad Spectrum SPF 20

Active Ingredient

Titanium Dioxide 6.45%

Purpose

Sunscreen

Uses

- helps prevent sunburn
- if used as directed with other sun protection measures (see decreases the risk of skin cancer and early skin aging caused by the sun. Directions),

Warnings

For external use only.

Do not use

on damaged or broken skin.

When using this product

keep out of eyes. Rinse with water to remove.

Stop use and ask a doctor if

rash occurs.

Keep out of reach of children.

If product is swallowed, get medical help or contact a Poison Control Center right away.

Directions

- Apply liberally 15 minutes before sun exposure
- Use a water resistant sunscreen if swimming or sweating
- Reapply at least every 2 hours
- Optional: apply to all skin exposed to the sun
- Spending time in the sun increases your risk of skin cancer and early skin aging. To decrease this risk, regularly use a sunscreen with a broad spectrum SPF of 15 or higher and other sun protection measures including: Sun Protection Measures.
-
  - limit time in the sun, especially from 10 a.m. - 2 p.m.
  - wear long-sleeve shirts, pants, hats, and sunglasses
  - Children under 6 months: Ask a doctor

Inactive Ingredients:

1,2-Hexanediol, Algae Extract, Allantoin, Alumina, Arginine, Bakuchiol, Butylene Glycol, Caprylic/Capric Triglyceride, Caprylyl Glycol, Caprylyl Methicone, Carbomer, Cetyl PEG/PPG-10/1 Dimethicone, Citrus Aurantium Amara (Bitter Orange) Flower Extract, Cyclopentasiloxane, Dimethicone/Vinyl Dimethicone Crosspolymer, Dipeptide-2, Dipotassium Glycyrrhizate, Disteardimonium Hectorite, Epilobium Angustifolium Extract, Glycereth-26, Glycerin, Helianthus Annuus (Sunflower) Seed Oil, Hesperidin Methyl Chalcone, Hydroxyethylcelluose, Iron Oxides (CI 77491), Iron Oxides (CI 77492), Iron Oxides (CI 77499), Isopropyl Titanium Triisostearate, Lactobacillus Ferment, Methicone, Mica, Neopentyl Glycol Dicaprate, Palmitoyl Oligopeptide, Palmitoyl Tetrapeptide-7, Panthenol, PEG/PPG-20/15 Dimethicone, PEG-10 Dimethicone, Polypropylsilsesquioxane, Polysorbate 20, Salicornia Herbacea Extract, Silica, Simmondsia Chinensis (Jojoba) Seed Extract, Sodium Chloride, Sodium PCA, Steareth-20, Tocopheryl Acetate, Triethoxycaprylylsilane, Trimethylsiloxysilicate, Undaria Pinnatifida Extract, Water/Aqua/Eau

Other information

- protect this product from excessive heat and direct sun

Questions or comments?

Call toll free 1-888-635-8884